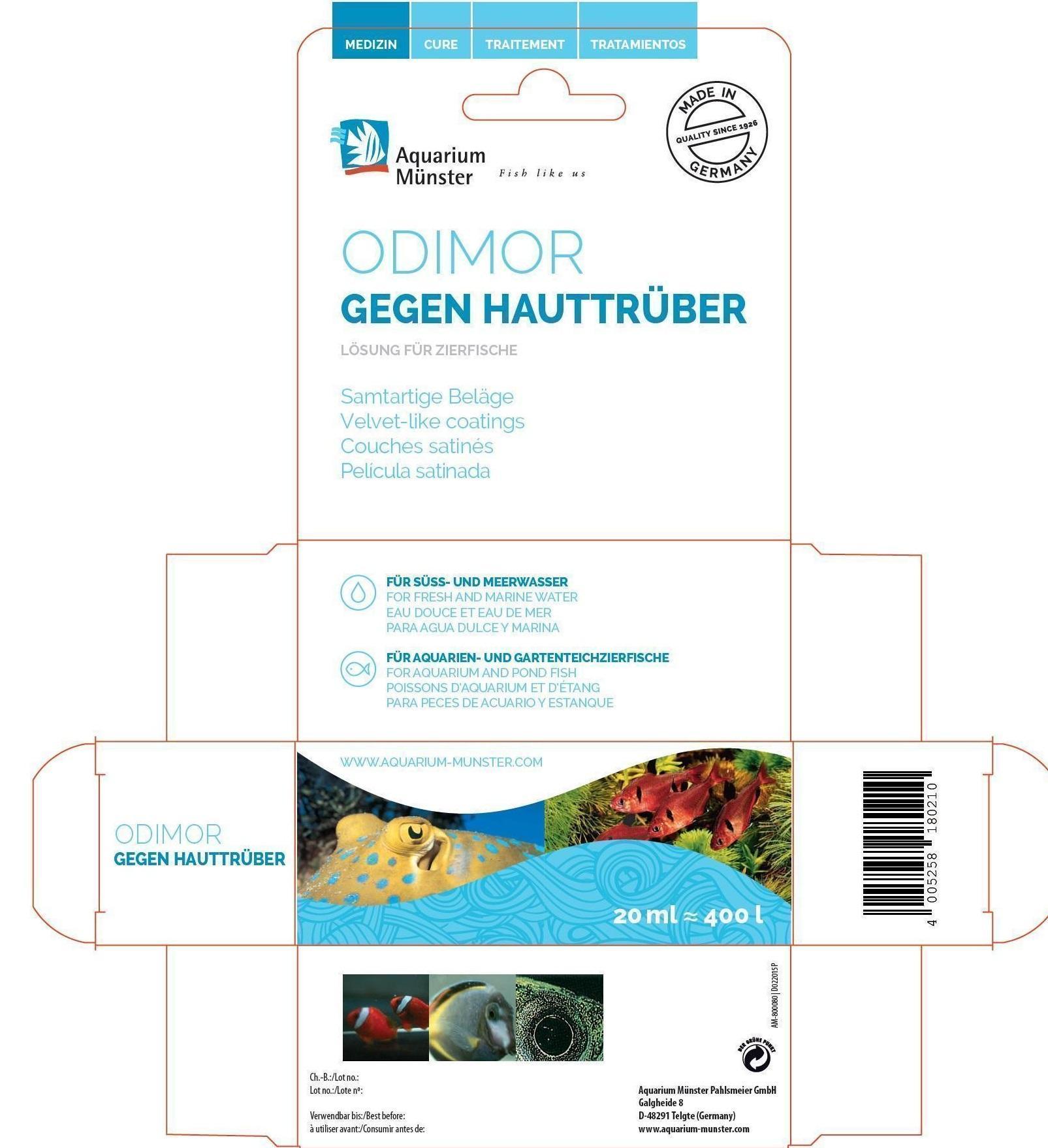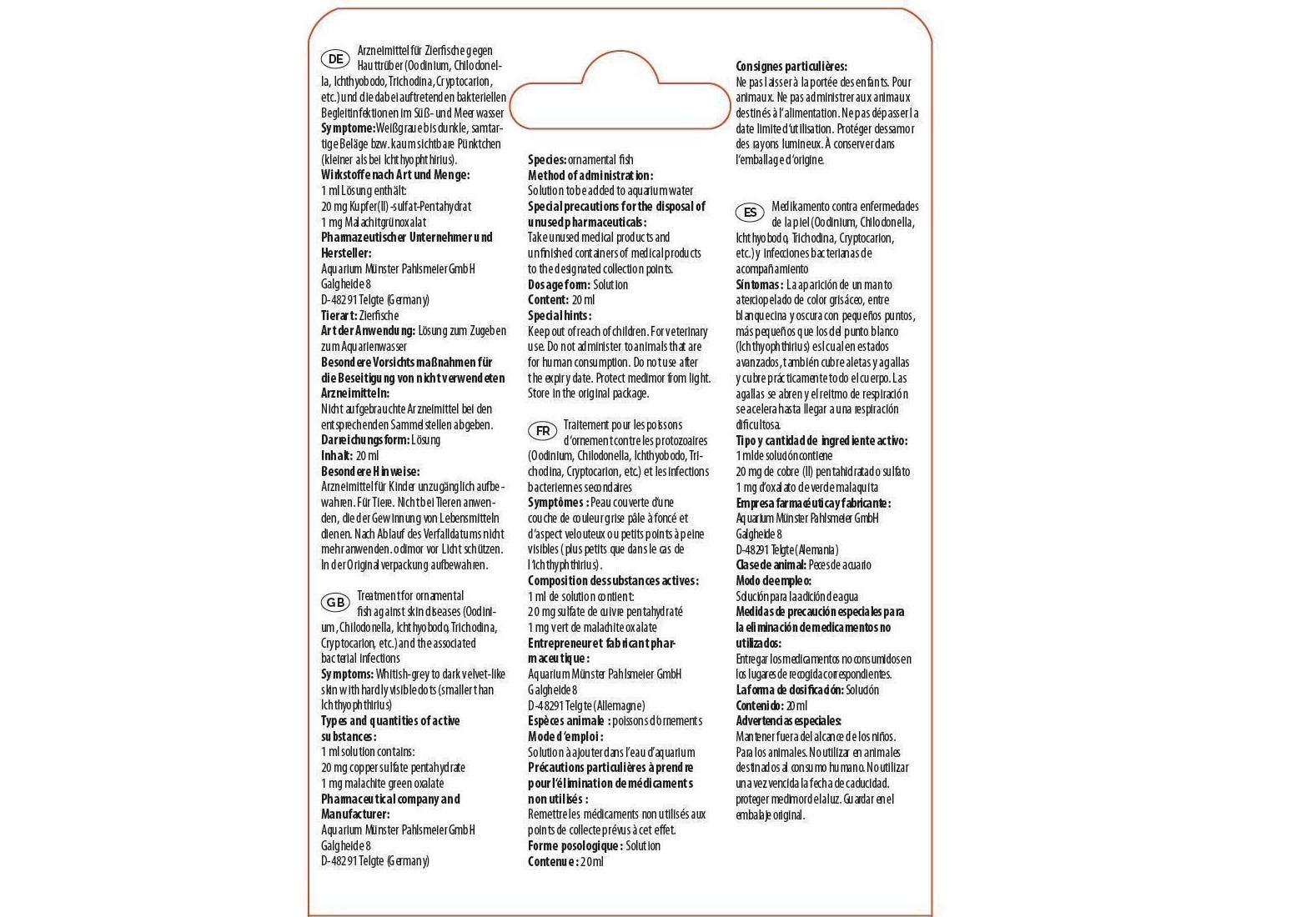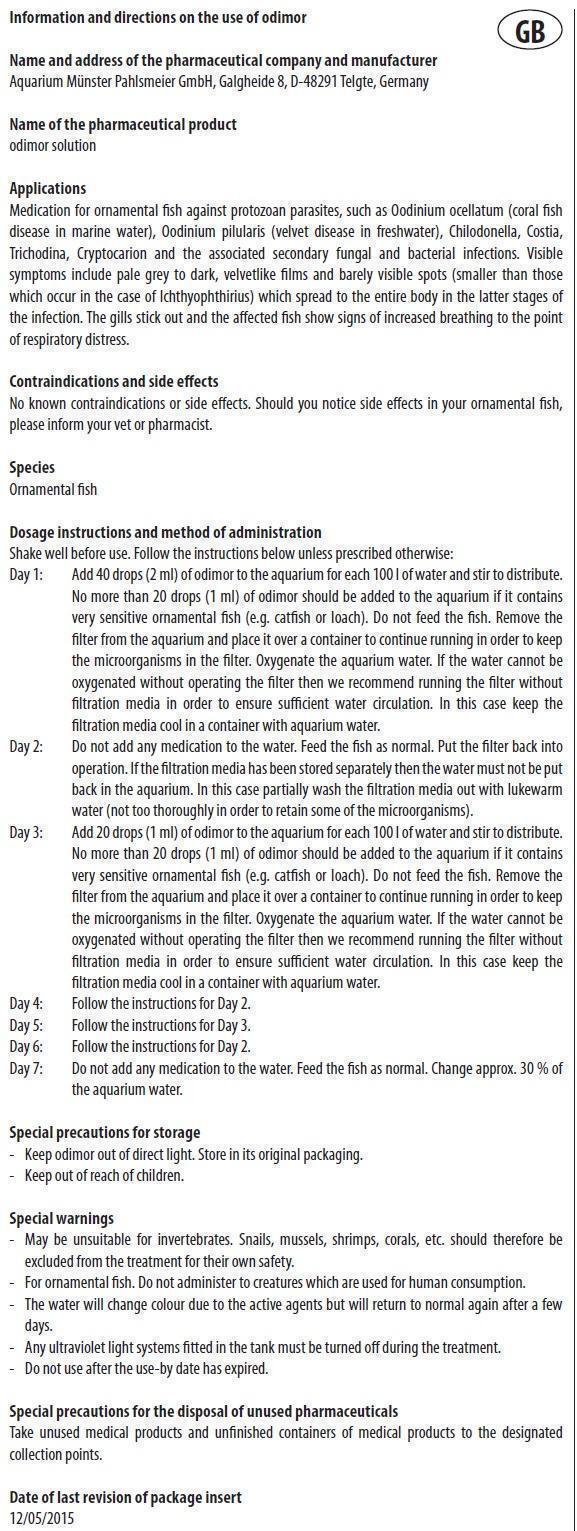 DRUG LABEL: ODIMOR
NDC: 86052-005 | Form: SOLUTION
Manufacturer: Aquarium Muenster Pahlsmeier GmbH
Category: animal | Type: OTC ANIMAL DRUG LABEL
Date: 20240419

ACTIVE INGREDIENTS: CUPRIC SULFATE 20 mg/1 mL; MALACHITE GREEN OXALATE 1 mg/1 mL

ODIMOR

Information and directions on the use of odimor

Name and address of the pharmaceutical company and manufacturer
Aquarium Münster Pahlsmeier GmbH, Galgheide 8, D-48291 Telgte, Germany

Name of the pharmaceutical product
odimor solution

Applications

Medication for ornamental fish against protozoan parasites, such as Oodinium ocellatum (coral fish disease in marine water), Oodinium pilularis (velvet disease in freshwater), Chilodonella, Costia, Trichodina, Cryptocarion and the associated secondary fungal and bacterial infections. Visible symptoms include pale grey to dark, velvetlike films and barely visible spots (smaller than those which occur in the case of Ichthyophthirius) which spread to the entire body in the latter stages of the infection. The gills stick out and the affected fish show signs of increased breathing to the point of respiratory distress.

Types and quantities of active substances:

1 ml solution contains:

20 mg copper sulfate pentahydrate

1 mg malachite green oxalate

Contraindications and side effects

No known contraindications or side effects. Should you notice side effects in your ornamental fish, please inform your vet or pharmacist.

Species

Ornamental fish

Dosage instructions and method of administration

Shake well before use. Follow the instructions below unless prescribed otherwise:
Day 1: Add 40 drops (2 ml) of odimor to the aquarium for each 100 l of water and stir to distribute. No more than 20 drops (1 ml) of odimor should be added to the aquarium if it contains very sensitive ornamental fish (e.g. catfish or loach). Do not feed the fish. Remove the
filter from the aquarium and place it over a container to continue running in order to keep the microorganisms in the filter. Oxygenate the aquarium water. If the water cannot be oxygenated without operating the filter then we recommend running the filter without filtration media in order to ensure sufficient water circulation. In this case keep the filtration media cool in a container with aquarium water.
Day 2: Do not add any medication to the water. Feed the fish as normal. Put the filter back into operation. If the filtration media has been stored separately then the water must not be put back in the aquarium. In this case partially wash the filtration media out with lukewarm
water (not too thoroughly in order to retain some of the microorganisms).
Day 3: Add 20 drops (1 ml) of odimor to the aquarium for each 100 l of water and stir to distribute. No more than 20 drops (1 ml) of odimor should be added to the aquarium if it contains very sensitive ornamental fish (e.g. catfish or loach). Do not feed the fish. Remove the
filter from the aquarium and place it over a container to continue running in order to keep the microorganisms in the filter. Oxygenate the aquarium water. If the water cannot be oxygenated without operating the filter then we recommend running the filter without
filtration media in order to ensure sufficient water circulation. In this case keep the filtration media cool in a container with aquarium water.
Day 4: Follow the instructions for Day 2.
Day 5: Follow the instructions for Day 3.
Day 6: Follow the instructions for Day 2.
Day 7: Do not add any medication to the water. Feed the fish as normal. Change approx. 30 % of the aquarium water.

Special precautions for storage

- Keep odimor out of direct light. Store in its original packaging.

- Keep out of reach of children.

Special warnings

- May be unsuitable for invertebrates. Snails, mussels, shrimps, corals, etc. should therefore be excluded from the treatment for their own safety.
- For ornamental fish. Do not administer to creatures which are used for human consumption.
- The water will change colour due to the active agents but will return to normal again after a few days.
- Any ultraviolet light systems fitted in the tank must be turned off during the treatment.

- Do not use after the use-by date has expired.

Special precautions for the disposal of unused pharmaceuticals

Take unused medical products and unfinished containers of medical products to the designated collection points.

Date of last revision of package insert
12/05/2015